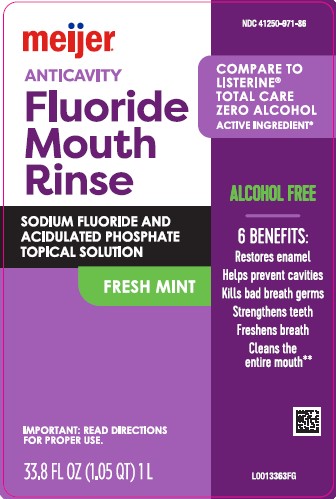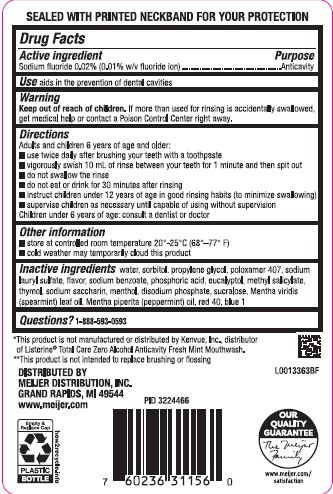 DRUG LABEL: Anticavity
NDC: 41250-971 | Form: RINSE
Manufacturer: Meijer, Inc.
Category: otc | Type: HUMAN OTC DRUG LABEL
Date: 20260224

ACTIVE INGREDIENTS: SODIUM FLUORIDE 0.1 mg/1 mL
INACTIVE INGREDIENTS: WATER; SORBITOL; PROPYLENE GLYCOL; POLOXAMER 407; SODIUM LAURYL SULFATE; SODIUM BENZOATE; PHOSPHORIC ACID; EUCALYPTOL; METHYL SALICYLATE; THYMOL; SACCHARIN SODIUM; MENTHOL, UNSPECIFIED FORM; SODIUM PHOSPHATE, DIBASIC, ANHYDROUS; SUCRALOSE; SPEARMINT OIL; PEPPERMINT OIL; FD&C RED NO. 40; FD&C BLUE NO. 1

Meijer 971.001/971AB
Burn-Free Fluoride Anti-Cavity Mouthwash

Tamper Evident Statement

Sealed With Printed Neckband For Your Protection

Active ingredient

Sodium fluoride 0.02% (0.01% w/v fluoride ion)

Purpose

Anticavity

Use

aids in the prevention of dental cavities

Warning

for this product

Keep out of Reach of Children.

If more than used for rinsing is accidentally swallowed, get medical help or contact a Poison Control Center right away.

Directions

Adults and children 6 years of age and older:

- use twice daily after brushing your teeth with a toothpaste
- vigorously swish 10 mL of rinse between your teeth for 1 miute and then spit out.
- do not swallow the rinse
- do not eat or drink for 30 minutes after rinsing
- instruct children under 12 years of age in good rinsing habits (to minimize swallowing)
- supervise children as necessary until capable of using without supervision

Children under 6 years of age: consult a dentist or doctor

Other information

- store at room temperature 20⁰-25⁰ C (68⁰-77⁰ F)
- cold weather may temporarily cloud this product

Inactive ingredients

water, sorbitol, propylene glycol, poloxamer 407, sodium lauryl sulfate, flavor, sodium benzoate, phosphoric acid, eucalyptol, methyl salicylate, thymol, sodium saccharin, menthol, disodium phosphate, sucralose, Mentha viridis (spearmint) leaf oil, Mentha piperita (peppermint) oil, red 40, blue 1

Questions?

1-888-593-0593

Disclaimers

*This product is not manufactured or distributed by Kenvue, Inc., distributor of Listerine®Total Care Zero Alcohol Anticavity Fresh Mint Mouthwash.

**This product is not intended to replace brushing or flossing

Adverse reactions section

DISTRIBUTED BY

MEIJER DISTRIBUTION, INC

GRAND RAPIDS, MI 49544

www.meijer.com

OUR QUALITY GUARANTEE

The Meijer Family

www.meijer.com/satisfaction

Empty & Replace Cap

PLASTIC BOTTLE

how2recycle.info

Principal display panel

NDC 41250-971-86

Compare to Listerine®Total Care Zero Alcohol Active Ingredient*

meijer®

ANTICAVITY

Fluoride Mouth Rinse

SODIUM FLUORIDE AND ACIDULATED PHOSPHATE TOPICAL SOLUTION

FRESH MINT

ALCOHOL FREE

6 BENEFITS:

Restores enamel

Helps prevent cavities

Kills bad breath germs

Strengthens teeth

Freshens breath

Cleans the entire mouth**

IMPORTANT: READ DIRECTIONS FOR PROPER USE.

33.8 FL OZ (1.05 QT) 1 L